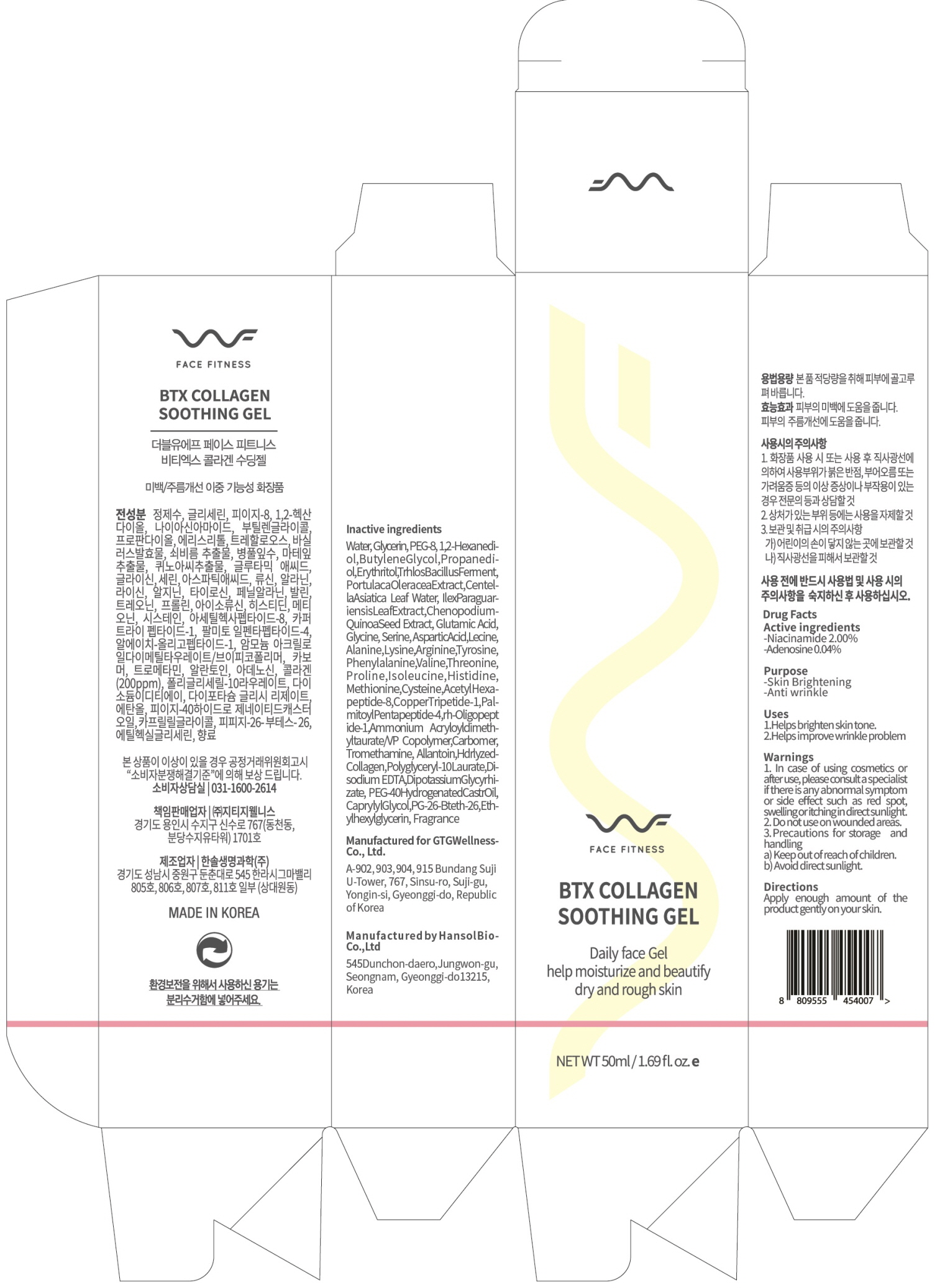 DRUG LABEL: WF FACE FITNESS BTX COLLAGEN SOOTHING
NDC: 71080-0014 | Form: GEL
Manufacturer: GTG Wellness Co., Ltd.
Category: otc | Type: HUMAN OTC DRUG LABEL
Date: 20200324

ACTIVE INGREDIENTS: Niacinamide 1.0 g/50 mL; Adenosine 0.02 g/50 mL
INACTIVE INGREDIENTS: Water; Glycerin

ACTIVE INGREDIENT

Active ingredients: Niacinamide 2.00%, Adenosine 0.04%

INACTIVE INGREDIENT

Inactive ingredients:

Water, Glycerin, PEG-8, 1,2-Hexanediol, Butylene Glycol, Propanediol, Erythritol, Trehalose, Bacillus Ferment, Portulaca Oleracea Extract, Centella Asiatica Leaf Water, Ilex Paraguariensis Leaf Extract, Chenopodium Quinoa Seed Extract, Glutamic Acid, Glycine, Serine, Aspartic Acid, Leucine, Alanine, Lysine, Arginine, Tyrosine, Phenylalanine, Valine, Threonine, Proline, Isoleucine, Histidine, Methionine, Cysteine, Acetyl Hexapeptide-8, Copper Tripeptide-1, Palmitoyl Pentapeptide-4, rh-Oligopeptide-1, Ammonium Acryloyldimethyltaurate/VP Copolymer, Carbomer, Tromethamine, Allantoin, Hydrolyzed Collagen, Polyglyceryl-10 Laurate, Disodium EDTA, Dipotassium Glycyrrhizate, PEG-40 Hydrogenated Castor Oil, Caprylyl Glycol, PPG-26-Buteth-26, Ethylhexylglycerin, Fragrance

PURPOSE

Purpose: Skin Brightening, Anti wrinkle

WARNINGS

1. In case of using cosmetics or after use, please consult a specialist if there is any abnormal symptom or side effect such as red spot, swelling or itching in direct sunlight.
2. Do not use on wounded areas.
3. Precautions for storage and handling
a) Keep out of reach of children.
b) Avoid direct sunlight.

KEEP OUT OF REACH OF CHILDREN

Uses

Helps brighten skin tone.
Helps improve wrinkle problem.

Directions

Apply enough amount of the product gently on your skin.